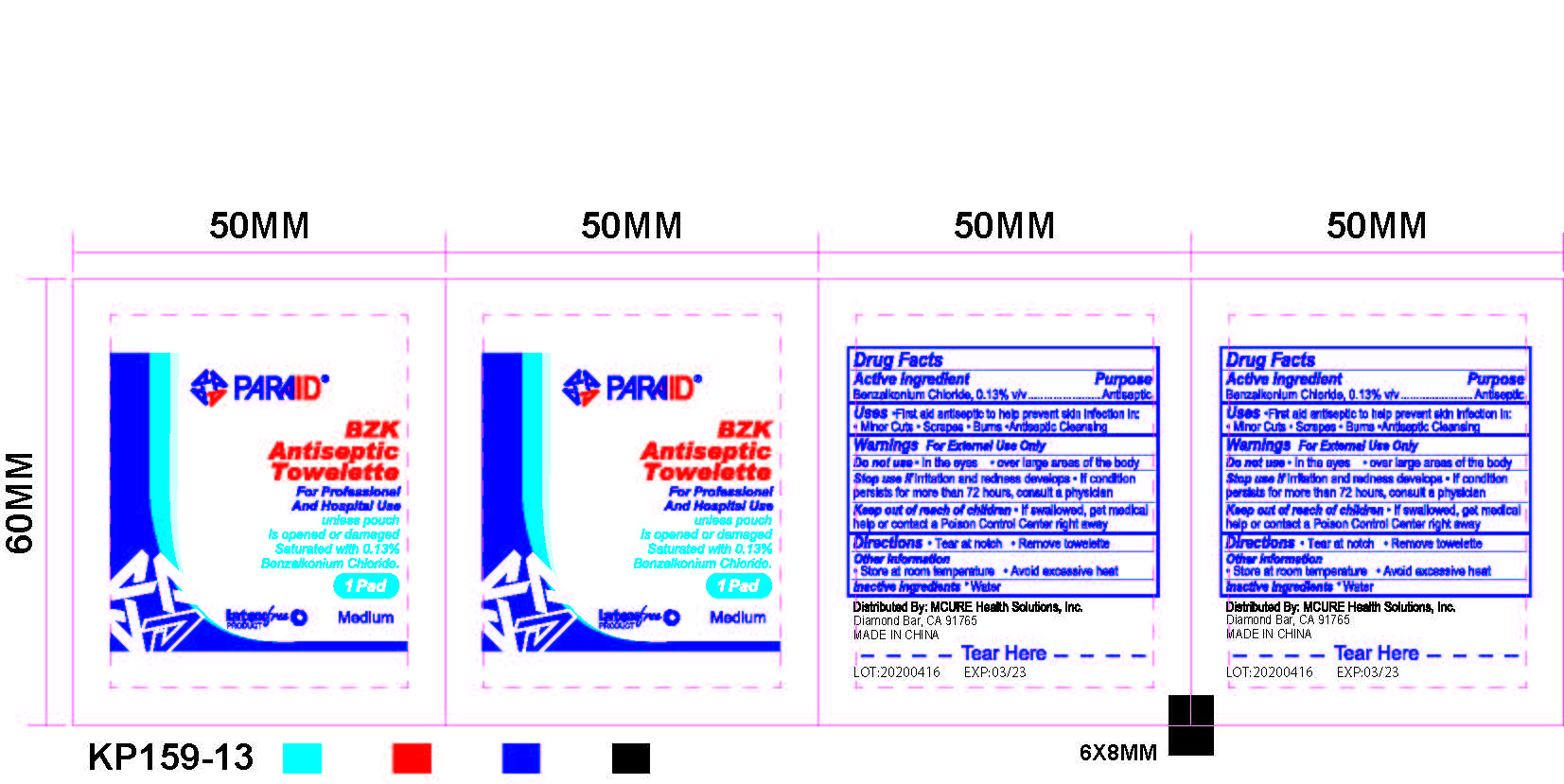 DRUG LABEL: BZK Antiseptic Towelette
NDC: 52486-610 | Form: CLOTH
Manufacturer: MCURE HEALTH SOLUTIONS INC.
Category: otc | Type: HUMAN OTC DRUG LABEL
Date: 20230322

ACTIVE INGREDIENTS: BENZALKONIUM CHLORIDE 0.13 g/100 g
INACTIVE INGREDIENTS: WATER

Active ingredient

Purpose - Benzalkonium Chloride 0.13% v/v....................Antiseptic

Uses

For handwashing to decrease bacteria on the skin

Warnings

For external use only.

Do not use

In the eyes. If this happens, rinse thoroughly with water.

Stop use and ask a doctor if irritation or redness develops and persists for more than 72 hours.

Keep out of reach of children. If swallowed, get medical help or contact a Poison Control Center right away.

Directions

- Tear open packet, unfold and use as a washcloth. Allow hands to dry without wiping.

Inactive ingredients

Water

DOSAGE AND ADMINISTRATION

Antiseptic Towelette

Sting-free